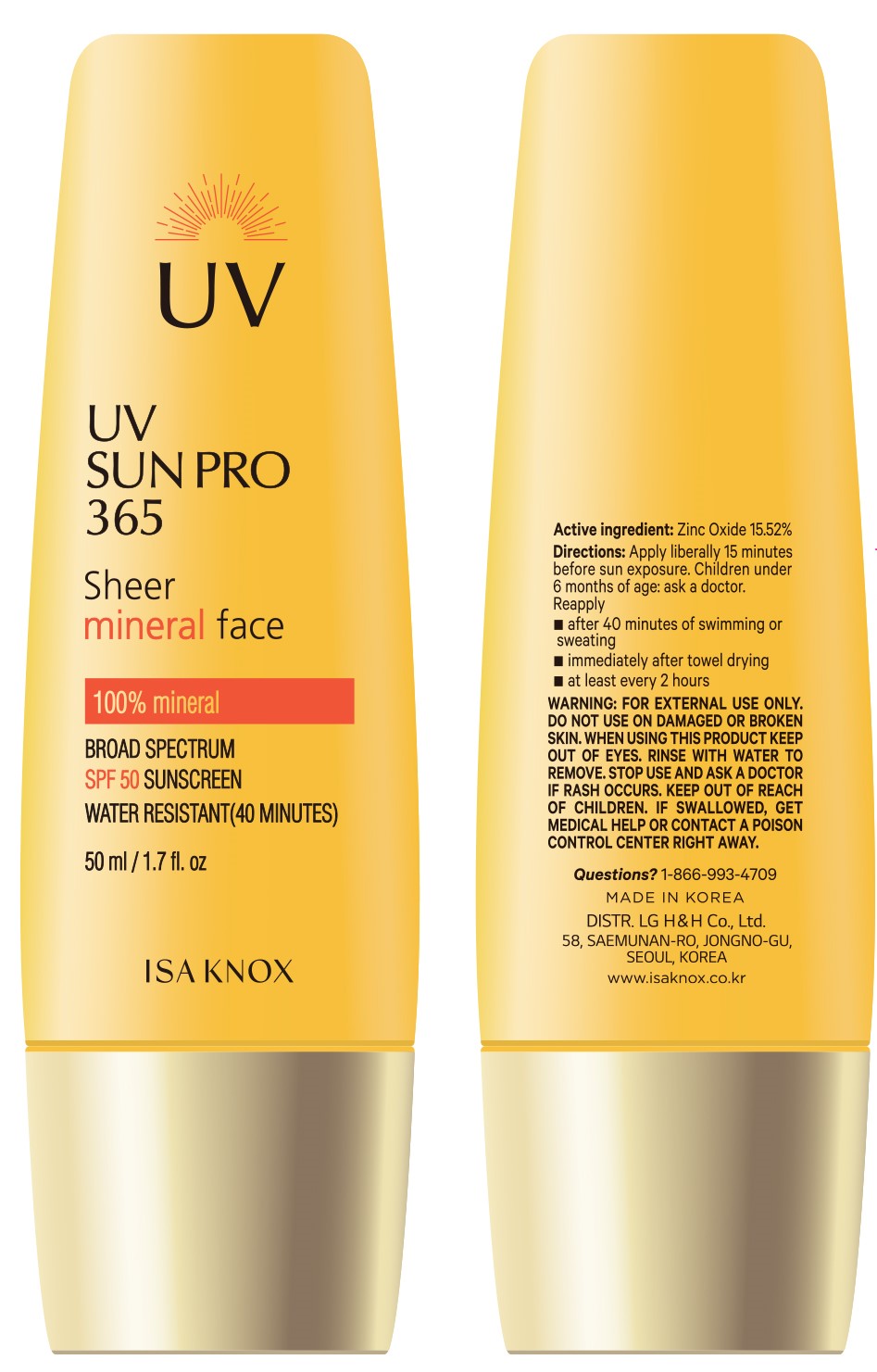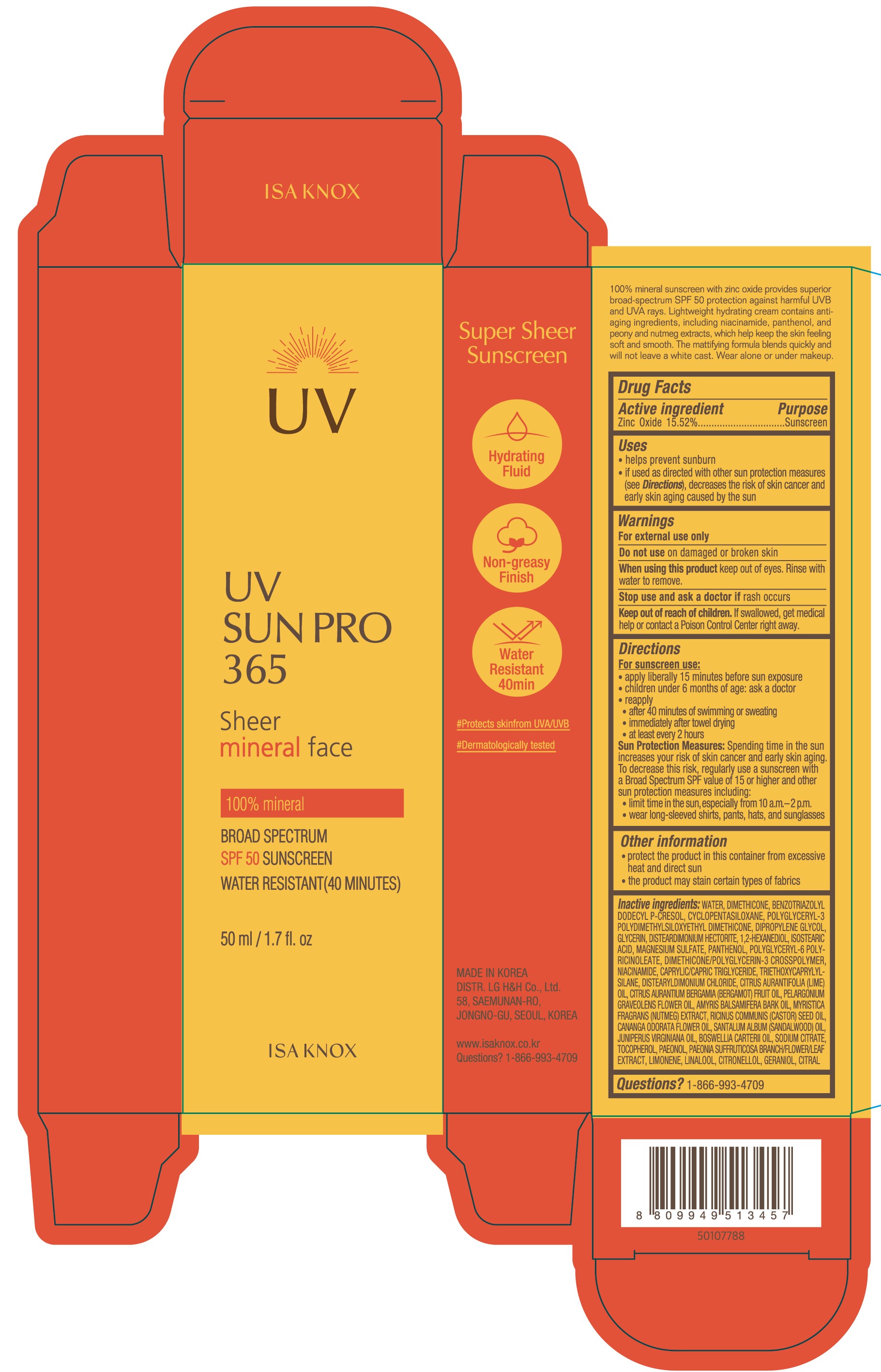 DRUG LABEL: ISA KNOX UV SUN PRO 365 Sheer Mineral Face
NDC: 53208-003 | Form: CREAM
Manufacturer: LG HOUSEHOLD & HEALTH CARE LTD.
Category: otc | Type: HUMAN OTC DRUG LABEL
Date: 20250408

ACTIVE INGREDIENTS: ZINC OXIDE 155.2 mg/1 mL
INACTIVE INGREDIENTS: CITRONELLOL; BENZOTRIAZOLYL DODECYL P-CRESOL; GLYCERIN; NIACINAMIDE; CAPRYLIC/CAPRIC TRIGLYCERIDE; CITRUS AURANTIUM BERGAMIA (BERGAMOT) FRUIT OIL; POLYGLYCERYL-6 POLYRICINOLEATE; AMYRIS BALSAMIFERA OIL; WATER; CYCLOPENTASILOXANE; DIPROPYLENE GLYCOL; SANTALUM ALBUM (SANDALWOOD) OIL; NUTMEG; DIMETHICONE; SODIUM CITRATE; PELARGONIUM GRAVEOLENS FLOWER OIL; CANANGA ODORATA FLOWER OIL; BOSWELLIA CARTERII OIL; TOCOPHEROL; LIMONENE, (+)-; LINALOOL; CITRAL; DISTEARYLDIMONIUM CHLORIDE; ISOSTEARIC ACID; DIMETHICONE/POLYGLYCERIN-3 CROSSPOLYMER; RICINUS COMMUNIS (CASTOR) SEED OIL; JUNIPERUS VIRGINIANA OIL; PAEONOL; DISTEARDIMONIUM HECTORITE; PANTHENOL; 1,2-HEXANEDIOL; MAGNESIUM SULFATE; TRIETHOXYCAPRYLYLSILANE; CITRUS AURANTIFOLIA (LIME) OIL; GERANIOL

Active ingredient

Zinc Oxide 15.52%

Purpose

Sunscreen

Uses

- helps prevent sunburn
- if used as directed with other sun protection measure (see Directions), decreases the risk of skin cancer and early skin aging caused by the sun

Warnings

For external use only

Do not use on damaged or broken skin

When using

When using this proudct keep out of eyes. Rinse with water to remove.

Keep out of reach of children.

Stop use

Stop use and ask a doctor if rash occurs

DOSAGE AND ADMINISTRATION

If swallowed, get medical help or contact a Poison Control Center right away.

Directions

For sunscreen use:

- apply liberally 15 minutes before sun exposure
- children under 6 months of age: ask a doctor
- reapply
  - after 40 minutes of swimming or sweating
  - immediately after towel drying
  - at least every 2 hours

Sun Protection Measures: Spending time in the sun increases your risk of skin cancer and early skin aging. To decrease this risk, regularly use a sunscreen with a Broad Spectrum SPF value of 15 or higher and other sun protection measures including:

- limit time in the sun, especially from 10 a.m.-2 p.m.
- wear long-sleeved shirts, pants, hats, and sunglasses

Other information

- protect the product in this container from excessive heat and direct sun
- the proudct may stain certain types of fabrics

Inactive Ingredients

WATER, DIMETHICONE, BENZOTRIAZOLYL DODECYL P-CRESOL, CYCLOPENTASILOXANE, POLYGLYCERYL-3 POLYDIMETHYLSILOXYETHYL DIMETHICONE, DIPROPYLENE GLYCOL, GLYCERIN, DISTEARDIMONIUM HECTORITE, 1,2-HEXANEDIOL, ISOSTEARIC ACID, MAGNESIUM SULFATE, PANTHENOL, POLYGLYCERYL-6 POLYRICINOLEATE, DIMETHICONE/POLYGLYCERIN-3 CROSSPOLYMER, NIACINAMIDE, CAPRYLIC/CAPRIC TRIGLYCERIDE, TRIETHOXYCAPRYLYLSILANE, DISTEARYLDIMONIUM CHLORIDE, CITRUS AURANTIFOLIA (LIME) OIL, CITRUS AURANTIUM BERGAMIA (BERGAMOT) FRUIT OIL, PELARGONIUM GRAVEOLENS FLOWER OIL, AMYRIS BALSAMIFERA BARK OIL, MYRISTICA FRAGRANS (NUTMEG) EXTRACT, RICINUS COMMUNIS (CASTOR) SEED OIL, CANANGA ODORATA FLOWER OIL, SANTALUM ALBUM (SANDALWOOD) OIL, JUNIPERUS VIRGINIANA OIL, BOSWELLIA CARTERII OIL, SODIUM CITRATE, TOCOPHEROL, PAEONOL, PAEONIA SUFFRUTICOSA BRANCH/FLOWER/LEAF EXTRACT, LIMONENE, LINALOOL, CITRONELLOL, GERANIOL, CITRAL

Questions?

1-866-993-4709